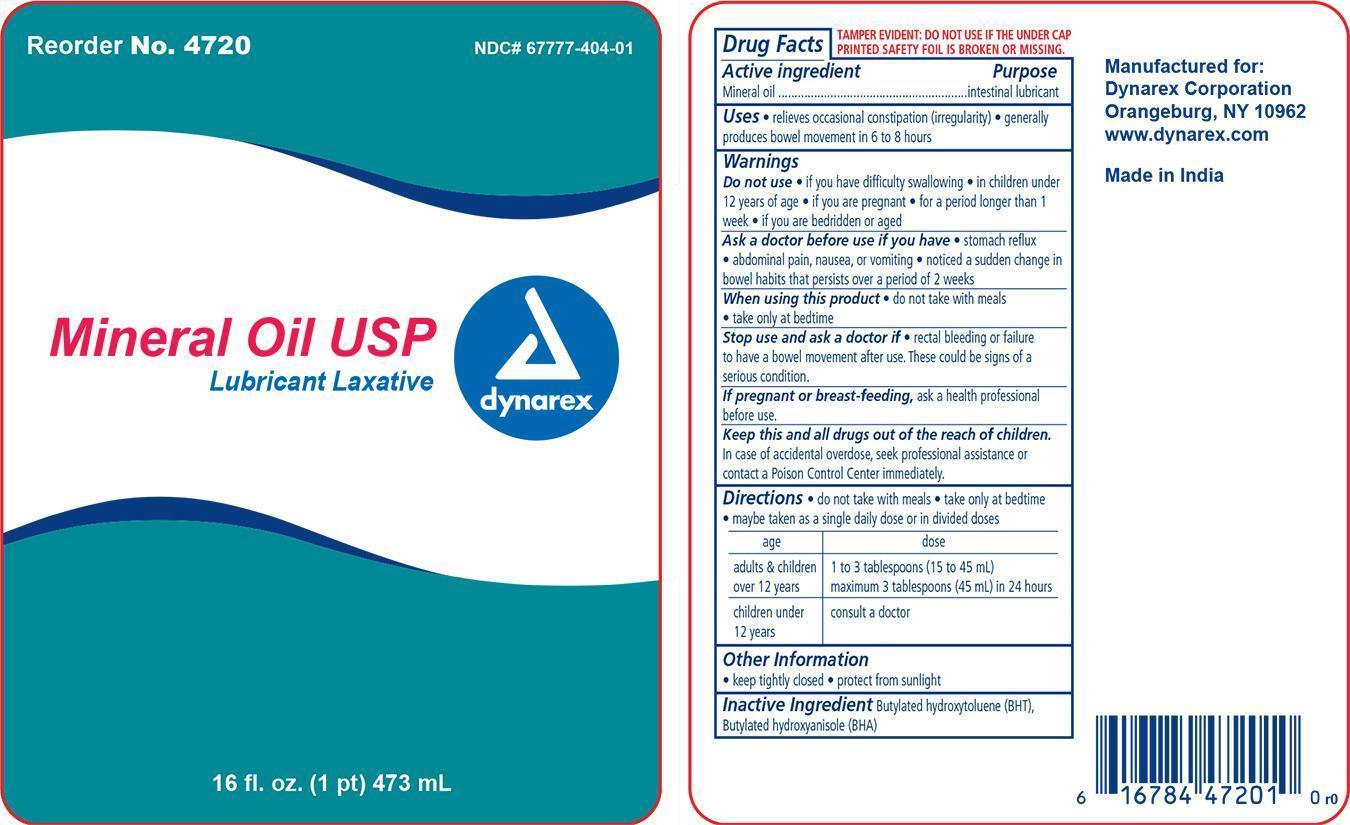 DRUG LABEL: DYNAREX LAXATIVE
NDC: 67777-404 | Form: LIQUID
Manufacturer: Dynarex Corporation
Category: otc | Type: HUMAN OTC DRUG LABEL
Date: 20140305

ACTIVE INGREDIENTS: MINERAL OIL 99 g/100 g
INACTIVE INGREDIENTS: butylated hydroxytoluene; Butylated hydroxyanisole

Dynarex Mineral Oil Laxative

Active Ingredient

Active Ingredient Purpose

Mineral oil Intestinal lubricant

Purpose

Relieves occassional constipation (irregularity).

Warnings

Do not use:

- If you have difficulty swallowing.
- In children under 12 years of age.
- If you are pregnant.
- For a period longer than 1 week.
- If you are bedridden or aged.

Indications & Usage

- For relief of occassional constipation (irregularity).

When using this product

- Do not take with meals
- Take only at bedtime

Ask a doctor before use if you have

- Stomach reflux
- Abdominal pain, nausea, or vomiting
- Notice a sudden change in bowel habits that persist over a period of 2 weeks

Stop use and ask a doctor if

- Rectal bleeding or failure to have a bowel movementafter use. These could be signs of a serious condition.

Dosage & Administration

Directions

- Do not take with meals
- Take only at bedtime
- May be taken as a single daily dose or in divided doses.

age | dose
adults and children; over 12 years | 1 to 3 tablespoons (15 to 45 ml); Maximum 3 tablespoons (45ml) in 24 hours
children under; 12 years | Consult a doctor

Keep Out Of Reach Of Children

- Keep this and all drugs out of the reach of children
- In case of accidental overdose, seek professional assistance or contact a Poison Control Center immediately.

Other information

- Keep tightly closed

- Protect from sunlight

Inactive ingredients

Inactive ingredients: Butylated hydroxytoluene (BHT), Butylated hydroxyanisole (BHA)

Principal Display Panel

Dynarex Mineral Oil Laxative
4270 Min oil.jpg